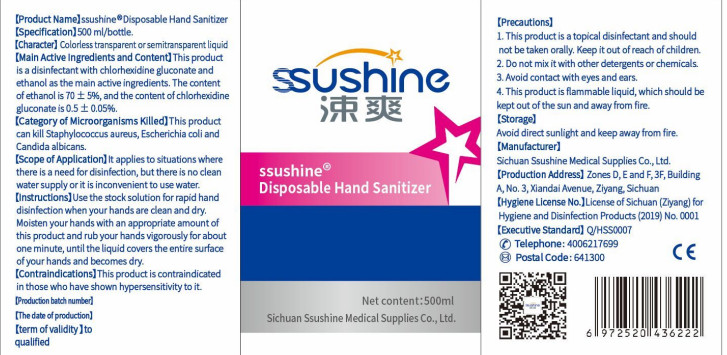 DRUG LABEL: Disposable hand sanitizer
NDC: 55480-002 | Form: LIQUID
Manufacturer: Sichuan Sushuang Medical Products Co., Ltd
Category: otc | Type: HUMAN OTC DRUG LABEL
Date: 20200418

ACTIVE INGREDIENTS: ALCOHOL 350 mL/500 mL
INACTIVE INGREDIENTS: CHLORHEXIDINE GLUCONATE; HYPROMELLOSES; GLYCERIN

DOSAGE AND ADMINISTRATION

Avoid direct sunlight and keep away from fire.

INACTIVE INGREDIENT

Glycerin

Hydroxyprpyl methyl cellulose

INDICATIONS AND USAGE

Use the stock solution for rapid hand disinfection when your hands are dean and dry.

ACTIVE INGREDIENT

Ethano

Chlorhexidine gluconate

keep out of children

PURPOSE

Disinfection
Sterilization
No Rinseing

WARNINGS

1. This product is a topical disinfectant and should not be taken oally. Kee it out of reach of children.
2. Do not mix it with other detergents or chemicals.
3. Awoid contact with eyes and ears.
4. This product is flammable liquid, which should be kept out of the sun and away from fire.